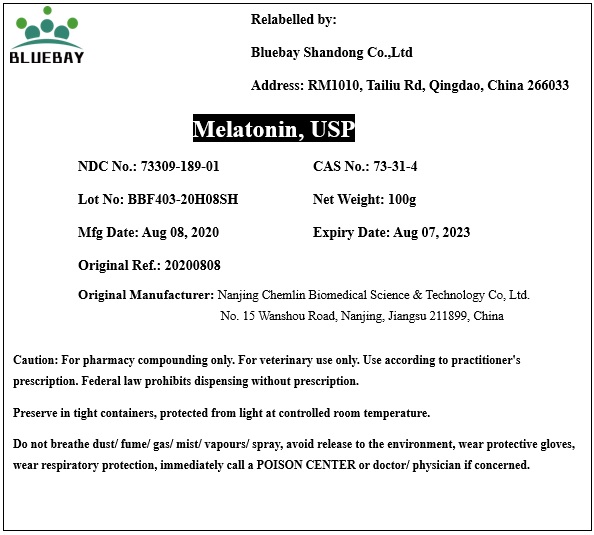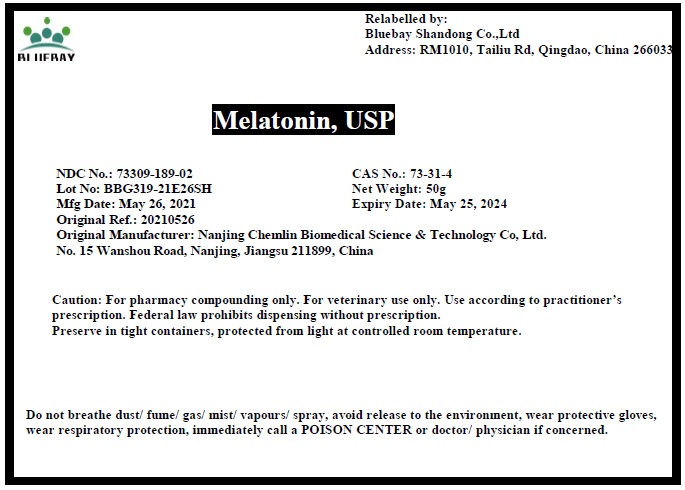 DRUG LABEL: Melatonin
NDC: 73309-189 | Form: POWDER
Manufacturer: BLUEBAY SHANDONG CO.,LTD
Category: other | Type: BULK INGREDIENT
Date: 20210617

ACTIVE INGREDIENTS: MELATONIN 1 g/1 g

Melatonin